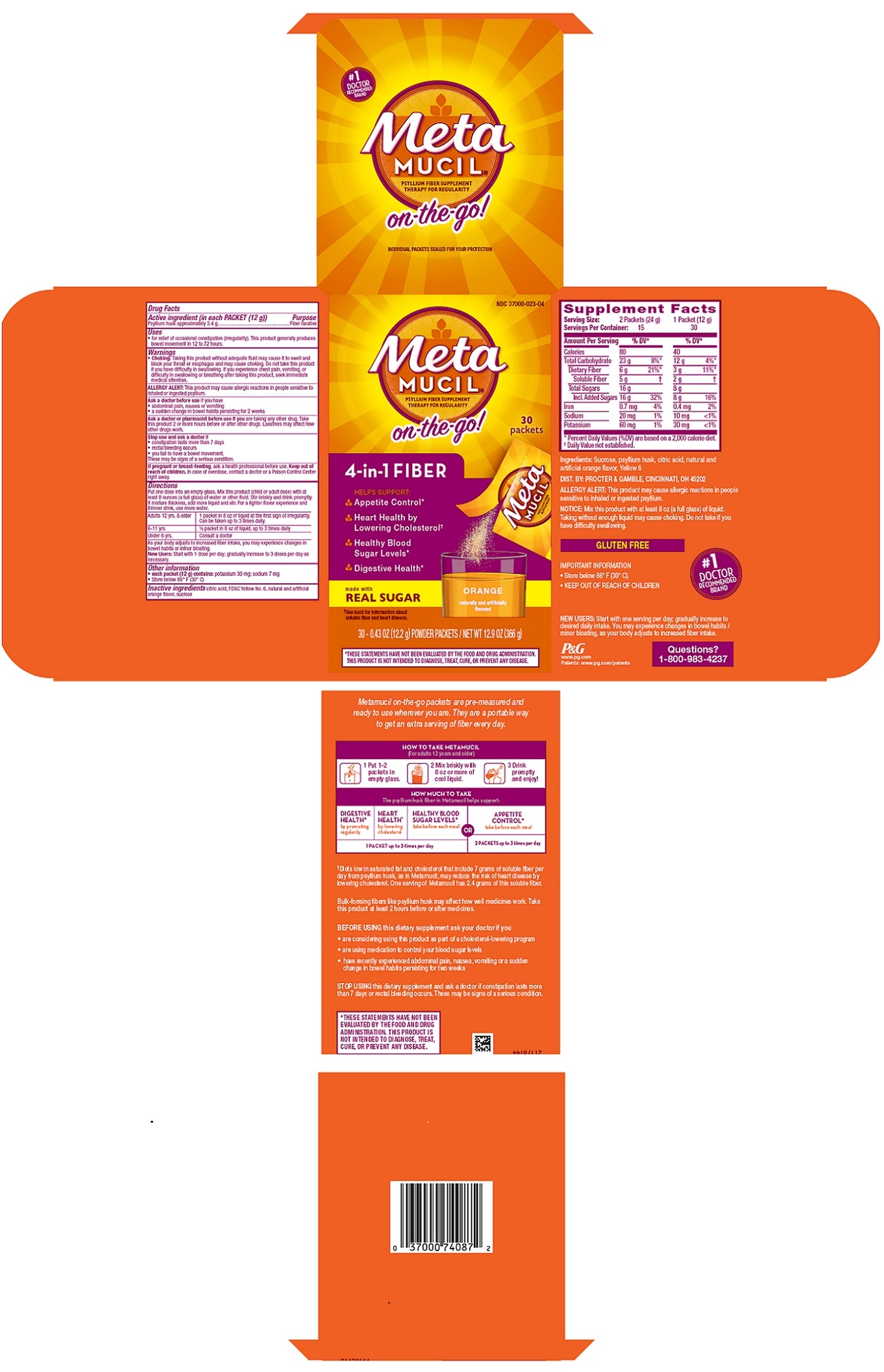 DRUG LABEL: Metamucil

NDC: 37000-023 | Form: POWDER
Manufacturer: The Procter & Gamble Manufacturing Company
Category: otc | Type: HUMAN OTC DRUG LABEL
Date: 20251202

ACTIVE INGREDIENTS: PSYLLIUM HUSK 3.4 g/12 g
INACTIVE INGREDIENTS: SUCROSE; FD&C YELLOW NO. 6; CITRIC ACID MONOHYDRATE

Metamucil® PSYLLIUM FIBER SUPPLEMENT THERAPY FOR REGULARITY

Drug Facts

Active ingredient (in each PACKET (12 g))

Psyllium husk approximately 3.4 g

Purpose

Fiber laxative

Uses

- for relief of occasional constipation (irregularity). This product generally produces bowel movement in 12 to 72 hours.

Warnings

Choking:

Taking this product without adequate fluid may cause it to swell and block your throat or esophagus andmay cause choking. Do not take this product if you have difficulty in swallowing. If you experience chest pain, vomiting, or difficulty in swallowing or breathing after taking this product, seek immediate medical attention.

ALLERGY ALERT:

This product may cause allergic reactions in people sensitive to inhaled or ingested psyllium.

Ask a doctor before use if you have

- abdominal pain, nausea or vomiting
- a sudden change in bowel habits persisting for 2 weeks

Ask a doctor or pharmacist before use if you

are taking any other drug. Take this product 2 or more hours before or after other drugs. Laxatives may affect how other drugs work.

Stop use and ask a doctor if

• constipation lasts more than 7 days
• rectal bleeding occurs
• you fail to have a bowel movement
These may be signs of a serious condition.

If pregnant or breast-feeding

ask a health professional before use.

Keep out of reach of children.

OVERDOSAGE

In case of overdose, contact a doctor or a PoisonControl Center right away.

Directions

Put one dose into an empty glass.Mix this product (child or adult dose) with at least 8 ounces (a full glass) of water or other fluid. Stir briskly and drink promptly. If mixture thickens, add more liquid and stir. For a lighter flavor experience and thinner drink, use more water.

Adults 12 yrs. & older | 1 packet in 8 oz of liquid at the first sign of irregularity. Can be taken up to 3 times daily.
6 – 11 yrs. | 1/2 packet in 8 oz of liquid, up to 3 times daily
Under 6 yrs. | Consult a doctor

As your body adjusts to increased fiber intake, you may experience changes in bowel habits or minor bloating.
New Users:Start with 1 dose per day; gradually increase to 3 doses per day as necessary.

Other information

• each packet contains: potassium 30 mg; sodium 7 mg
• Store below 86° F (30° C)

Inactive ingredients

citric acid, FD&C Yellow No. 6, natural and artificial orange flavor, sucrose

Questions?

1-800-983-4237

INDIVIDUAL PACKETS SEALED FOR YOUR PROTECTION

DIST. BY PROCTER & GAMBLE

CINCINNATI, OH 45202

PRINCIPAL DISPLAY PANEL

MetaMUCIL®

PSYLLIUM FIBER SUPPLEMENT THERAPY FOR REGULARITY

on-the-go!

30 packets

4-in-1 FIBER

HELPS SUPPORT:

Appetite Control*
Heart Health by Lowering Cholesterol†
Healthy Blood Sugar Levels*
Digestive Health*

made with REAL SUGAR

ORANGE

naturally and artificially flavored

†See back for information about soluble fiber and heart disease

30 - 0.43 OZ (12.2 g) POWDER PACKETS/NET WT 12.9 OZ (366 g)

*These statements have not been evaluated by the Food and Drug Administration. This product is not intended to diagnose, treat, cure, or prevent any disease.